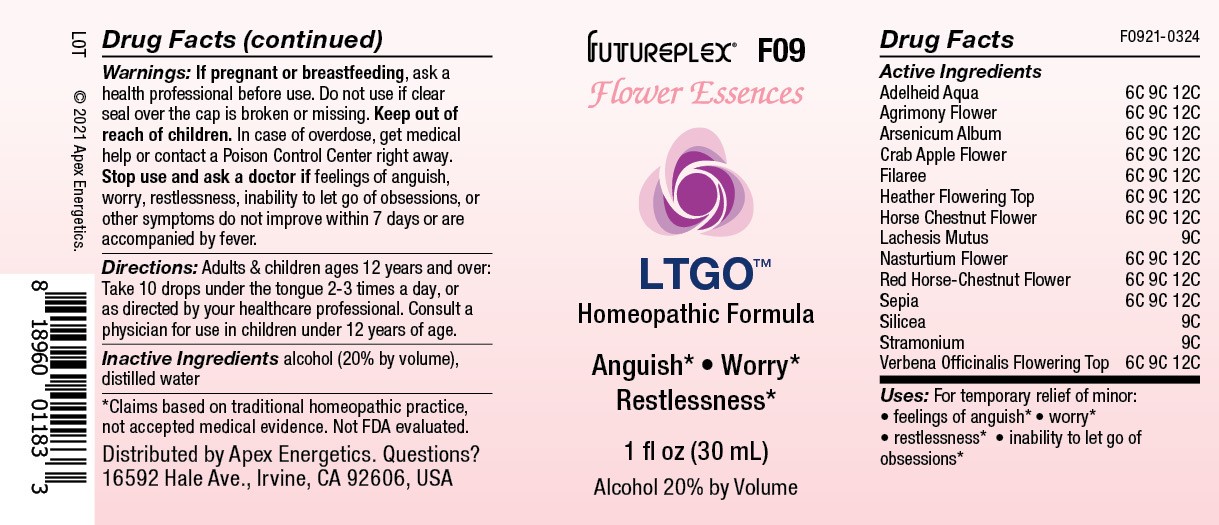 DRUG LABEL: F09
NDC: 63479-0609 | Form: SOLUTION/ DROPS
Manufacturer: Apex Energetics Inc.
Category: homeopathic | Type: HUMAN OTC DRUG LABEL
Date: 20240108

ACTIVE INGREDIENTS: ARSENIC TRIOXIDE 12 [hp_C]/1 mL; ERODIUM CICUTARIUM 12 [hp_C]/1 mL; CALLUNA VULGARIS FLOWERING TOP 12 [hp_C]/1 mL; AESCULUS HIPPOCASTANUM FLOWER 12 [hp_C]/1 mL; LACHESIS MUTA VENOM 9 [hp_C]/1 mL; VERBENA OFFICINALIS FLOWERING TOP 12 [hp_C]/1 mL; WATER 12 [hp_C]/1 mL; AGRIMONIA EUPATORIA FLOWER 12 [hp_C]/1 mL; TROPAEOLUM MAJUS FLOWER 12 [hp_C]/1 mL; SEPIA OFFICINALIS JUICE 12 [hp_C]/1 mL; DATURA STRAMONIUM 9 [hp_C]/1 mL; AESCULUS X CARNEA FLOWER 12 [hp_C]/1 mL; SILICON DIOXIDE 9 [hp_C]/1 mL; MALUS SYLVESTRIS FLOWER 12 [hp_C]/1 mL
INACTIVE INGREDIENTS: ALCOHOL

F09

Active Ingredients
Adelheid Aqua | 6C 9C 12C
Agrimony Flower | 6C 9C 12C
Arsenicum Album | 6C 9C 12C
Crab Apple Flower | 6C 9C 12C
Filaree | 6C 9C 12C
Heather Flowering Top | 6C 9C 12C
Horse Chestnut Flower | 6C 9C 12C
Lachesis Mutus | 9C
Nasturtium Flower | 6C 9C 12C
Red Horse-Chestnut Flower | 6C 9C 12C
Sepia | 6C 9C 12C
Silicea | 9C
Stramonium | 9C
Verbena Officinalis Flowering Top | 6C 9C 12C

INDICATIONS AND USAGE

Uses:

For temporary relief of minor:

feelings of anguish*

worry*

restlessness*

inability to let go of obsessions*

*Claims based on traditional homeopathic practice, not accepted medical evidence. Not FDA evaluated.

Warnings:

PREGNANCY OR BREAST FEEDING

If pregnant or breastfeeding, ask a health professional before use.

Do not use if clear seal over the cap is broken or missing.

Keep out of reach of children. In case of overdose, get medical help or contact a Poison Control Center right away.

Stop use and ask a doctor if feelings of anguish, worry, restlessness, inability to let go of obsessions, or other symptoms do not improve within 7 days or are accompanied by fever.

Directions:

Adults & children ages 12 years and over: Take 10 drops under the tongue 2-3 times a day, or as directed by your healthcare professional. Consult a physician for use in children under 12 years of age.

Inactive Ingredients

alcohol (20% by volume), distilled water

Distributed by Apex Energetics. Questions?

16592 Hale Ave., Irvine, CA 92606, USA

PACKAGE LABEL

FUTUREPLEX® F09

Flower Essences

LTGO™

Homeopathic Formula

Anguish*

Worry*

Restlessness*

1 fl oz (30 mL)

Alcohol 20% by Volume